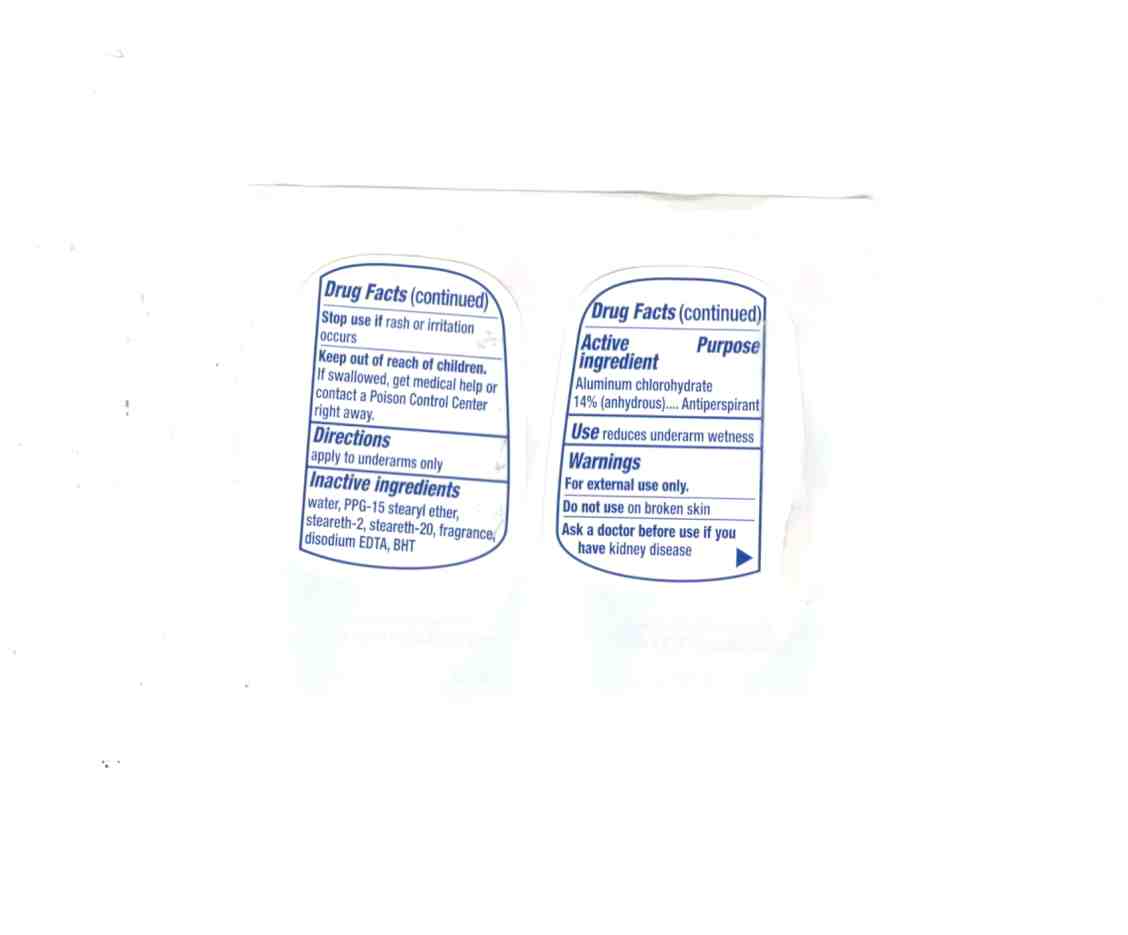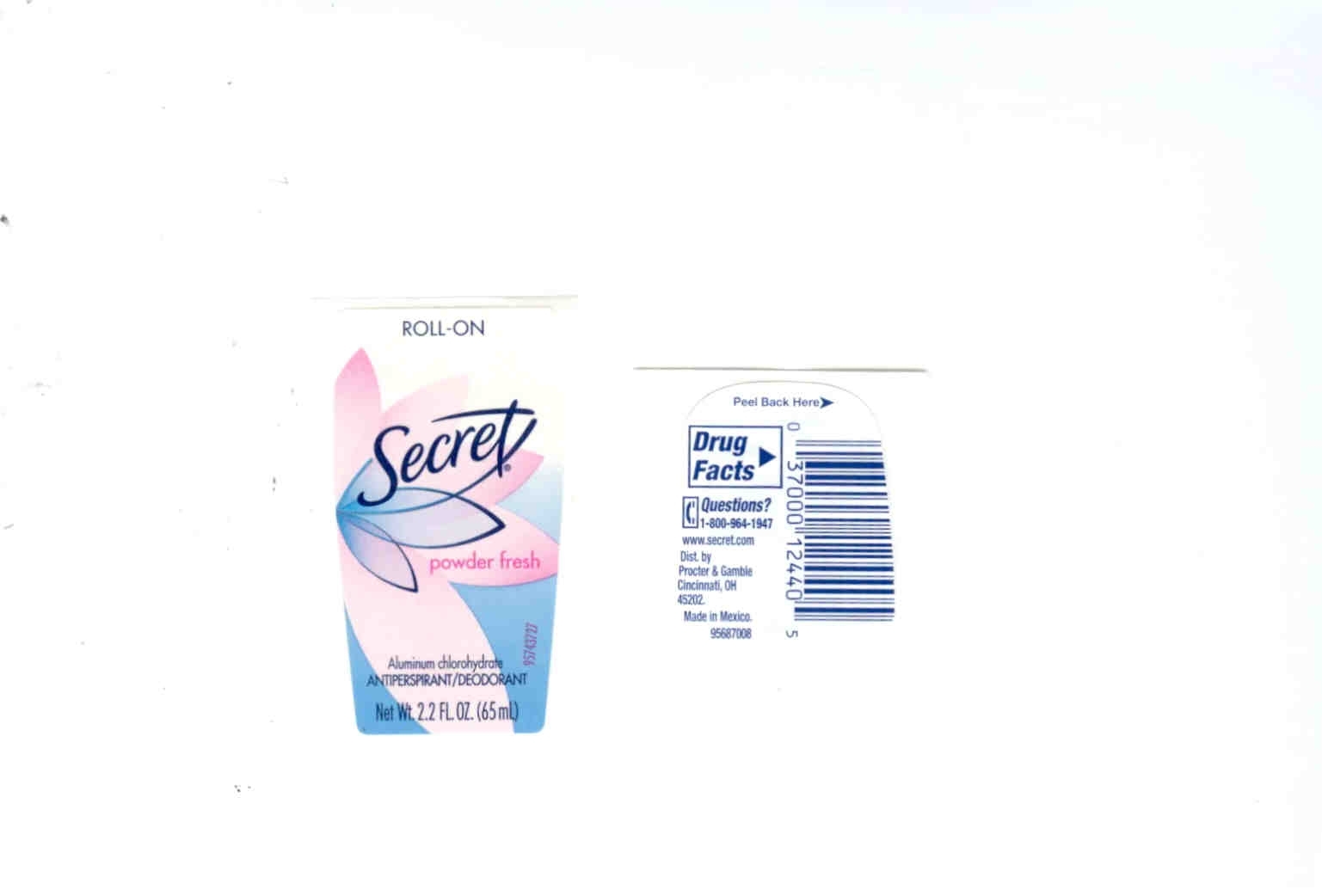 DRUG LABEL: Secret AP Roll On Deo Powder Fresh
NDC: 61962-4490 | Form: SOLUTION
Manufacturer: Aerobal S.A. De C.V.
Category: otc | Type: HUMAN OTC DRUG LABEL
Date: 20101005

ACTIVE INGREDIENTS: Aluminum Chlorohydrate 36 mL/65 mL
INACTIVE INGREDIENTS: water; STEARETH-20; DISODIUM 2,2'-DIHYDROXY-4,4'-DIMETHOXY-5,5'-DISULFOBENZOPHENONE; STEARYL ETHYLHEXANOATE; STEARETH-2

Secret AP Roll On Deoderant Powder Fresh

ACTIVE INGREDIENT

Aluminum chlorohydrate 14% (anhydrous)

INACTIVE INGREDIENT

water, PPG-15 stearyl ether, steareth-2, steareth-20, fragrance, disodium EDTA, BHT

DOSAGE AND ADMINISTRATION

Apply to underarms only

INDICATIONS AND USAGE

Reduces underarm weatness

keep out of reach of children. if swallowed, get medical help or contact a poison control center right away.

Stop use if rash or irritation occurs.

For external use only.

Do not use on broken skin.

Asak a doctor before use if you have kidney disease.

PURPOSE

Antiperspirant/deoderant

PACKAGE LABEL

Roll on, Secret powder fresh.